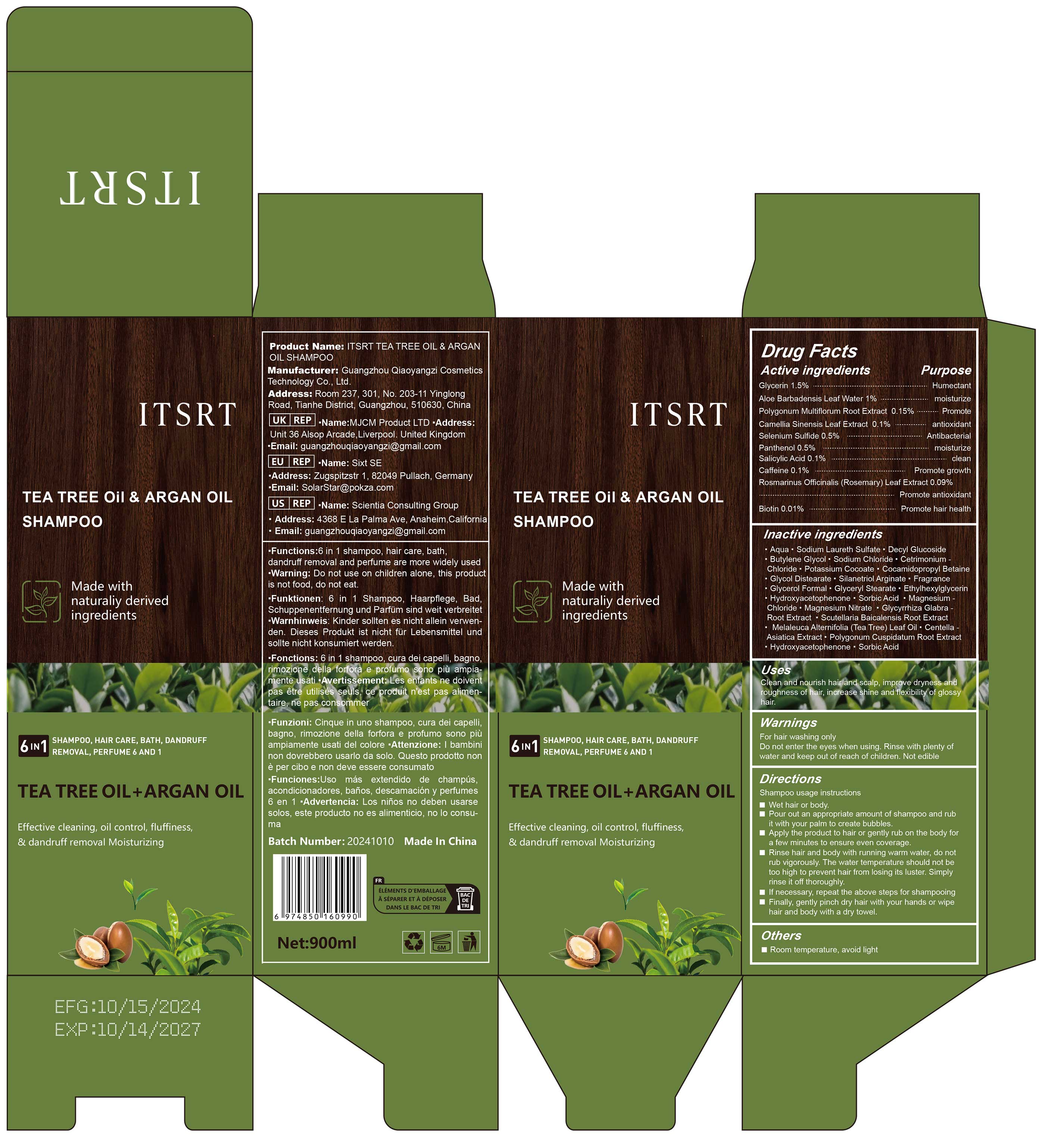 DRUG LABEL: ITSRT Tea Tree Oil and Argan Oil
NDC: 84751-095 | Form: LIQUID
Manufacturer: Guangzhou Qiaoyangzi Cosmetics Technology Co Ltd
Category: otc | Type: HUMAN OTC DRUG LABEL
Date: 20241030

ACTIVE INGREDIENTS: CAFFEINE 0.1 mg/500 mL; PANTHENOL 0.5 mg/500 mL; GLYCERIN 1.5 mg/500 mL; ALOE VERA LEAF 1 mg/500 mL; GREEN TEA LEAF 0.1 mg/500 mL; ROSEMARY 0.09 mg/500 mL; BIOTIN 0.01 mg/500 mL; FALLOPIA MULTIFLORA ROOT 0.15 mg/500 mL; SELENIUM SULFIDE 0.5 mg/500 mL; SALICYLIC ACID 0.1 mg/500 mL
INACTIVE INGREDIENTS: WATER 71.65 mg/500 mL

Active ingredlents

Selenium Sulfide 0.50%

Salicylic Acid 0.10%

Biotin 0.01%

Rosmarinus Officinalis (Rosemary) Leaf Extract 0.09%

Caffeine 0.10%

Panthenol 0.50%

Camellia Sinensis Leaf Extract 0.100%

Polygonum Multiflorum Root Extract 0.150%

Aloe Barbadensis Leaf Water 1.000%

Glycerin 1.500%

Purpose

Shampoo

Hair Care

Body Wash / Bathing

Dandruff Control

Hair Loss Prevention

Fragrance

Uses

Directions
Shampoo usage instructions
Wet hair or body.Pour out an appropriate amount of shampoo and rubit with your palm to create bubbles.Apply the product to hair or gently rub on the body fora few minutes to ensure even coverage.
Rinse hair and body with running warm water, do notrub vigorously. The water temperature should not betoo high to prevent hair from losing its luster. Simplyrinse it off thoroughly.
If necessary, repeat the above steps for shampooingFinally, gently pinch dry hair with your hands or wipehair and body with a dry towel.

Wamings

For external use only. Avoid contact with eyes. If irritation occurs, discontinue use.

Stop use

If irritation, redness, or discomfort occurs, discontinue use immediately and consult a doctor.

Do not use

Allergy to Ingredients: Do not use if you have an allergic reaction to any ingredient in this product.
Skin Damage or Inflammation: Do not use if there is any skin damage, inflammation, or infection during use.
Eye Contact: Avoid contact with eyes; if contact occurs, rinse immediately with water and seek medical help.
Use by Children: Do not use in children under 12 years old unless directed by a doctor.
Pregnancy or Breastfeeding: Consult a doctor before use if you are pregnant or breastfeeding.

Keep out of reach of children!

Keep away from children!
Use by Children: Do not use in children under 12 years old unless directed by a parent or doctor.

Precautions for Use

Eye Contact: Avoid contact with eyes; if contact occurs, rinse immediately with water and seek medical help.

INACTIVE INGREDIENT SECTON

Aqua 71.650%
Sodium Laureth Sulfate 8.300%
Decyl Glucoside 2.000%
Butylene Glycol 2.000%
Sodium Chloride 1.750%
Cetrimonium Chloride 1.650%
Potassium Cocoate 1.500%
Cocamidopropyl Betaine 1.500%
Glycol Distearate 1.000%
Silanetriol Arginate 1.000%
Fragrance 0.500%
Glycerol Formal 0.500%
Glyceryl Stearate 0.500%
Ethylhexylglycerin 0.500%
Hydroxyacetophenone 0.350%
Sorbic Acid 0.300%
Magnesium Chloride 0.100%
Magnesium Nitrate 0.100%
Glycyrrhiza Glabra Root Extract 0.30%
Scutellaria Baicalensis Root Extract 0.30%
Melaleuca Alternifolia (Tea Tree) Leaf Oil 0.05%
Centella Asiatica Extract 0.05%
Polygonum Cuspidatum Root Extract 0.05%

Instructions for Use

Wet Hair: Thoroughly wet your hair and scalp before using the shampoo.

Dispense the Right Amount: Squeeze out an appropriate amount of shampoo (usually about the size of a coin), adjusting the amount based on the length and thickness of your hair.

Apply Evenly: Apply the shampoo evenly to your hair and scalp, gently massaging to create lather.

Rinse: Rinse thoroughly with warm water, ensuring that all the shampoo is washed out.

Repeat if Necessary: If you have special cleansing needs, you may use the shampoo again.

Follow with Conditioner: After using the shampoo, it is recommended to use a conditioner to keep your hair moisturized and smooth.

Frequency of Use: It is advisable to use the shampoo regularly based on your hair type and needs. Typically, using it 2-3 times a week is appropriate.

DOSAGE & ADMINISTRATION SECTION

Frequently Asked Questions

How often should I use ITSRT?
You only need to use ITSRT every 3 to 4 days (about twice a week) for 8 weeks. On the days you don’t use ITSRT, you can use your regular shampoo and conditioner.

Can I continue to use ITSRT?
Always follow the label instructions. You may use ITSRT every 3 to 4 days (about twice a week) for 8 weeks, then as needed to control dandruff.

Is ITSRT safe to use on color-treated or keratin-treated hair?
Yes, ITSRT is safe to use on color-treated, chemically processed, and gray hair.

Is it okay to use a conditioner with ITSRT?
We recommend using a conditioner between uses of ITSRT. Some dandruff shampoos don’t smell very good; how does ITSRT smell? ITSRT has a clean, fresh scent and a pearlescent, soft look and feel.

Does ITSRT work on severe dandruff?
Clinical studies show that ITSRT is effective in controlling symptoms of mild, moderate, and even severe dandruff, such as flaking, dryness, and itching.

How fast does ITSRT work?
Always follow the label instructions and use ITSRT every 3 to 4 days (about twice a week) for 8 weeks. Published clinical study results show that ketoconazole, the active ingredient in ITSRT, starts working from the first use to relieve dandruff symptoms and control the fungus that causes dandruff.